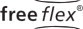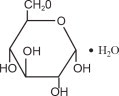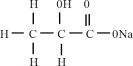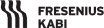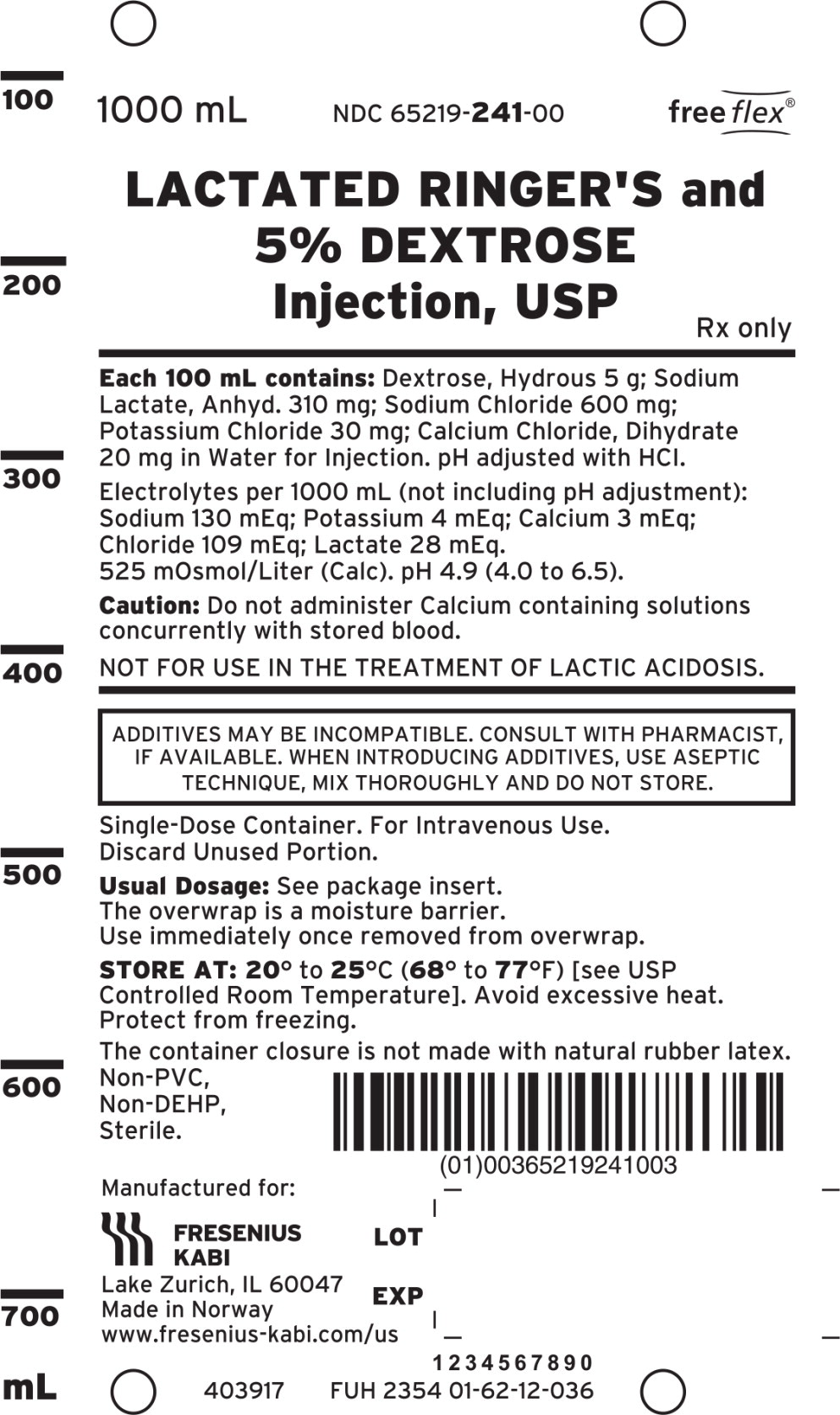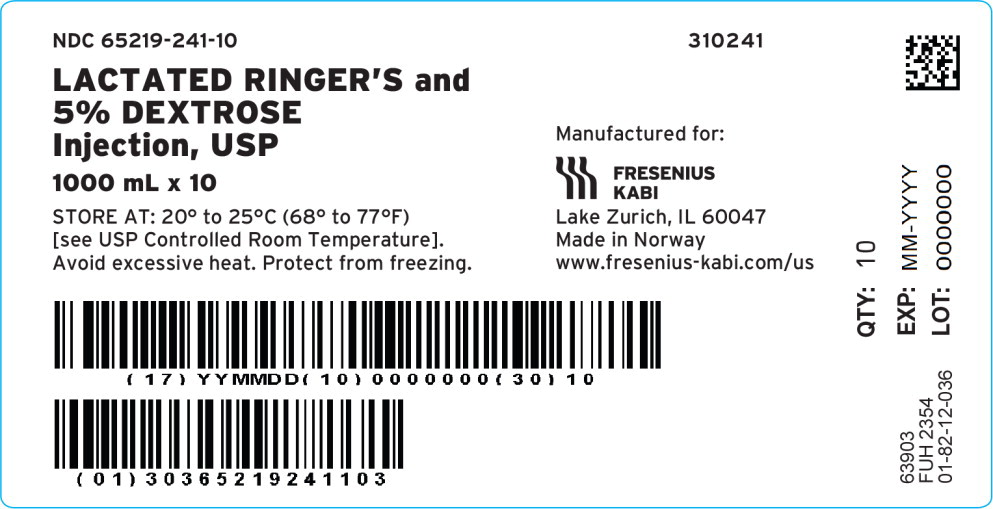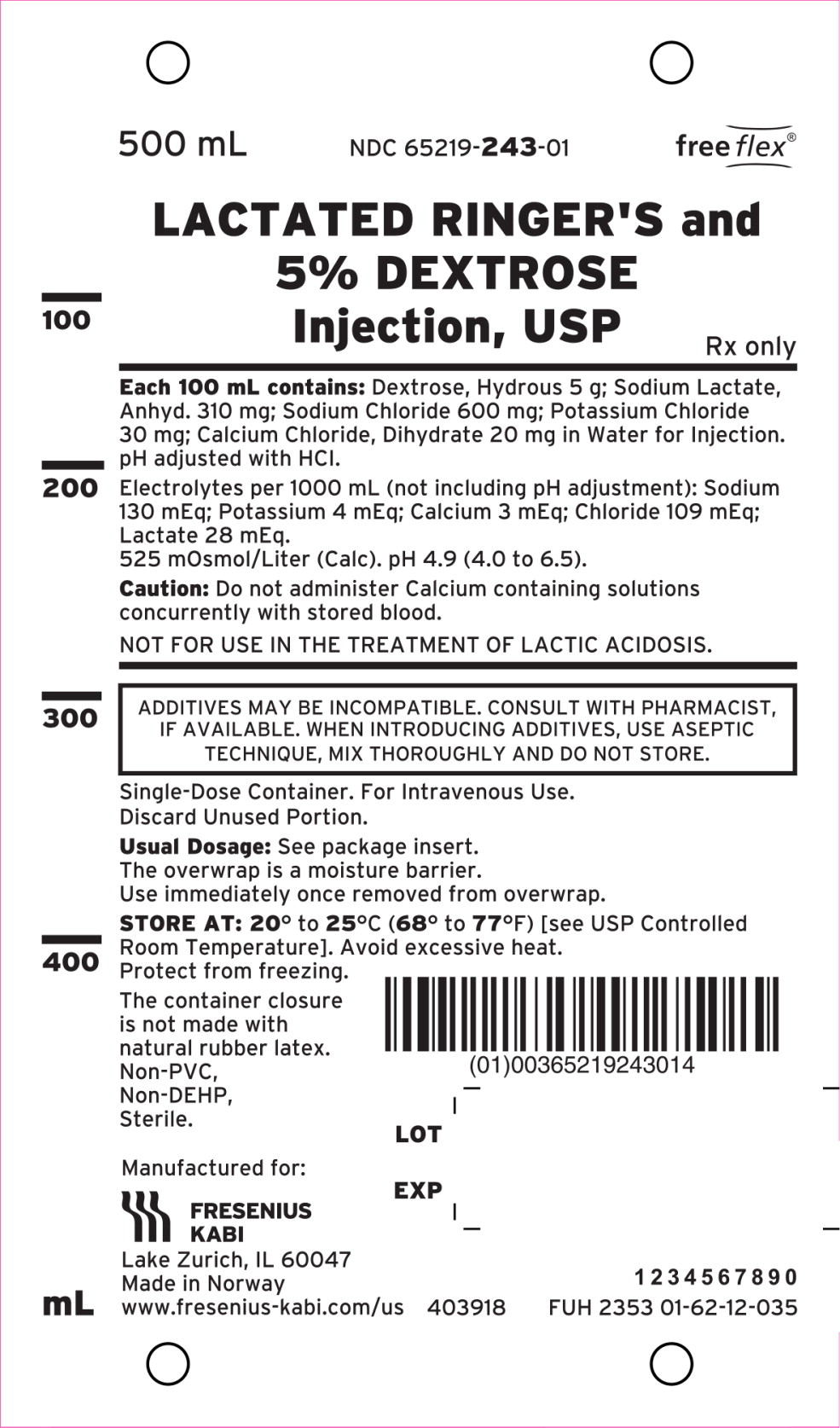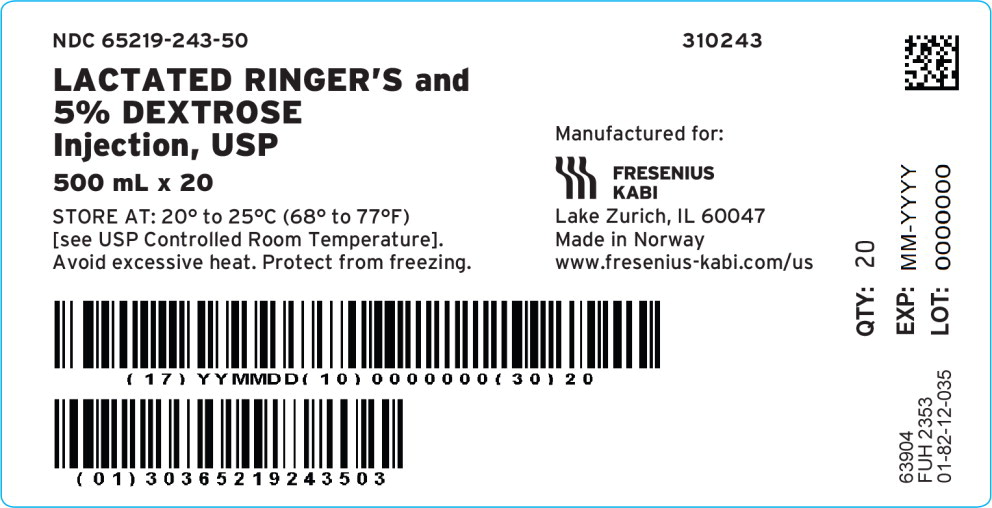 DRUG LABEL: Lactated Ringers and Dextrose

NDC: 65219-241 | Form: INJECTION, SOLUTION
Manufacturer: Fresenius Kabi USA, LLC

Category: prescription | Type: HUMAN PRESCRIPTION DRUG LABEL
Date: 20240522

ACTIVE INGREDIENTS: SODIUM CHLORIDE
 600 mg/100 mL; SODIUM LACTATE
 310 mg/100 mL; POTASSIUM CHLORIDE
 30 mg/100 mL; CALCIUM CHLORIDE
 20 mg/100 mL; DEXTROSE MONOHYDRATE
 5 g/100 mL
INACTIVE INGREDIENTS: HYDROCHLORIC ACID; Water

LACTATED RINGER'S AND 5% DEXTROSE INJECTION, USP

Flexible Plastic Container

Rx only

DESCRIPTION

The product is sterile, nonpyrogenic solution containing isotonic concentration of electrolytes with dextrose in water for injection. The solutions containing dextrose and electrolytes are hypertonic. They are administered by intravenous infusion for parenteral replacement of extracellular losses of fluid and electrolytes, with minimal carbohydrate calories.

Each 100 mL of Lactated Ringer's and 5% Dextrose Injection, USP contains dextrose, hydrous 5 g, sodium chloride 600 mg, sodium lactate, anhydrous 310 mg, potassium chloride 30 mg and calcium chloride, dihydrate 20 mg. Contains only hydrochloric acid for pH adjustment. A liter provides 179 calories (from dextrose and lactate), sodium (Na^+), 130 mEq, potassium (K^+) 4 mEq, calcium (Ca^++) 3 mEq, chloride (Cl^−) 109 mEq and lactate [CH3CH(OH) COO−] 28 mEq and has a hypertonic osmolar concentration of 525 mOsmol (calc.). The pH is 4.9 (4.0 − 6.5).

The solution contains no bacteriostat, antimicrobial agent or added buffer (except for pH adjustment) and is intended only for use as a single-dose injection. When smaller doses are required the unused portion should be discarded.

This solution is a parenteral fluid, nutrient and/or electrolyte replenishers.

Dextrose, USP is chemically designated D-glucose, monohydrate (C6H12O6 • H2O), a hexose sugar freely soluble in water.

It has the following structural formula:

Calcium Chloride, USP is chemically designated calcium chloride dihydrate (CaCl2 • 2 H2O), white fragments or granules freely soluble in water.

Potassium Chloride, USP is chemically designated KCl, a white granular powder freely soluble in water.

Sodium Chloride, USP is chemically designated NaCl, a white crystalline powder freely soluble in water.

Sodium Lactate, USP is chemically designated monosodium lactate [CH3CH(OH)COONa], a 50% aqueous solution miscible in water.

It has the following structural formula:

Water for Injection, USP is chemically designated H2O.

The flexible plastic container is fabricated from a specially formulated non-plasticized, film containing polypropylene and thermoplastic elastomers (freeflex® bag). Water can permeate from inside the container into the overwrap but not in amounts sufficient to affect the solution significantly. Solutions inside the plastic container also can leach out certain of their chemical components in very small amounts before the expiration period is attained. However, the safety of the plastic has been confirmed by tests in animals according to USP biological standards for plastic containers.

CLINICAL PHARMACOLOGY

When administered intravenously, these solutions provide sources of water and electrolytes with minimal carbohydrate calories. Their electrolyte content resembles that of the principal ionic constituents of normal plasma and the solutions therefore are suitable for parenteral replacement of extracellular losses of fluid and electrolytes, with carbohydrate calories.

Solutions containing carbohydrate in the form of dextrose restore blood glucose levels and provide calories.

Carbohydrate in the form of dextrose may aid in minimizing liver glycogen depletion and exerts a protein-sparing action. Dextrose injected parenterally undergoes oxidation to carbon dioxide and water.

Calcium chloride in water dissociates to provide calcium (Ca^++) and chloride (Cl^-) ions. They are normal constituents of the body fluids and are dependent on various physiologic mechanisms for maintenance of balance between intake and output. Approximately 80% of body calcium is excreted in the feces as insoluble salts; urinary excretion accounts for the remaining 20%.

Potassium chloride in water dissociates to provide potassium (K^+) and chloride (Cl^-) ions. Potassium is found in low concentration in plasma and extracellular fluids (3.5 to 5.0 mEq/liter in a healthy adult). It is the chief cation of body cells (160 mEq/liter of intracellular water). Potassium plays an important role in electrolyte balance. Normally about 80 to 90% of the potassium intake is excreted in the urine; the remainder in the stools and to a small extent, in the perspiration. The kidney does not conserve potassium well so that during fasting or in patients on a potassium-free diet, potassium loss from the body continues resulting in potassium depletion.

Sodium chloride in water dissociates to provide sodium (Na^+) and chloride (Cl^-) ions. Sodium (Na^+) is the principal cation of the extracellular fluid and plays a large part in the therapy of fluid and electrolyte disturbances. Chloride (Cl^-) has an integral role in buffering action when oxygen and carbon dioxide exchange occurs in the red blood cells. The distribution and excretion of sodium (Na^+) and chloride (Cl^-) are largely under the control of the kidney which maintains a balance between intake and output.

Sodium lactate provides (Na^+) and lactate (C3 H5 O3^-) ions. The lactate anion is in equilibrium with pyruvate and has an alkalizing effect resulting from simultaneous removal by the liver of lactate and hydrogen ions. In the liver, lactate is metabolized to glycogen which is ultimately converted to carbon dioxide and water by oxidative metabolism. The sodium (Na^+) ion combines with bicarbonate ion produced from carbon dioxide of the body and thus retains bicarbonate to combat metabolic acidosis (bicarbonate deficiency). The normal plasma level of lactate ranges from 0.9 to 1.9 mEq/liter.

Water is an essential constituent of all body tissues and accounts for approximately 70% of total body weight. Average normal adult daily requirement ranges from two to three liters (1.0 to 1.5 liters each for insensible water loss by perspiration and urine production).

Water balance is maintained by various regulatory mechanisms. Water distribution depends primarily on the concentration of electrolytes in the body compartments and sodium (Na^+) plays a major role in maintaining physiologic equilibrium.

INDICATIONS AND USAGE

These solutions are indicated for parenteral replacement of extracellular losses of fluid and electrolytes, with minimal carbohydrate calories, as required by the clinical condition of the patient.

CONTRAINDICATIONS

Solutions containing lactate are NOT FOR USE IN THE TREATMENT OF LACTIC ACIDOSIS.

WARNINGS

Solutions containing calcium ions should not be administered simultaneously through the same administration set as blood because of the likelihood of coagulation.

Solutions which contain potassium should be used with great care, if at all, in patients with hyperkalemia, severe renal failure and in conditions in which potassium retention is present.

Solutions containing sodium ions should be used with great care, if at all, in patients with congestive heart failure, severe renal insufficiency and in clinical states in which there exists edema with sodium retention.

In patients with diminished renal function, administration of solutions containing sodium or potassium ions may result in sodium or potassium retention.

Solutions containing lactate ions should be used with great care in patients with metabolic or respiratory alkalosis. The administration of lactate ions should be done with great care where there is an increased level or an impaired utilization of lactate ions, as in severe hepatic insufficiency.

The intravenous administration of these solutions can cause fluid and/or solute overloading resulting in dilution of serum electrolyte concentrations, overhydration, congested states or pulmonary edema. The risk of dilutional states is inversely proportional to the electrolyte concentrations of administered parenteral solutions.

The risk of solute overload causing congested states with peripheral and pulmonary edema is directly proportional to the electrolyte concentrations of such solutions.

PRECAUTIONS

Clinical evaluation and periodic laboratory determinations are necessary to monitor changes in fluid balance, electrolyte concentrations and acid-base balance during prolonged parenteral therapy or whenever the condition of the patient warrants such evaluation.

Solutions containing dextrose should be used with caution in patients with known subclinical or overt diabetes mellitus.

Caution must be exercised in the administration of parenteral fluids, especially those containing sodium ions, to patients receiving corticosteroids or corticotropin.

Potassium containing solutions should be used with caution in the presence of cardiac disease, particularly in digitalized patients or in the presence of renal disease.

Solutions containing lactate ions should be used with caution as excess administration may result in metabolic alkalosis.

Do not administer unless solution is clear and container is undamaged. Discard unused portion.

PREGNANCY

Pregnancy Animal reproduction studies have not been conducted with Ringer's Injection, USP, Ringer's and Dextrose Injection, USP, Lactated Ringer's Injection, USP or Lactated Ringer's and Dextrose Injection, USP. It is also not known whether these injections can cause fetal harm when administered to a pregnant woman or can affect reproduction capacity. These injections should be given to a pregnant woman only if clearly needed.

PEDIATRIC USE

Pediatric Use The safety and effectiveness in the pediatric population are based on the similarity of the clinical conditions of the pediatric and adult populations. In neonates or very small infants the volume of fluid may affect fluid and electrolyte balance.

Frequent monitoring of serum glucose concentrations is required when dextrose is prescribed to pediatric patients, particularly neonates and low birth weight infants.

In very low birth weight infants, excessive or rapid administration of dextrose injection may result in increased serum osmolarity and possible intracerebral hemorrhage.

ADVERSE REACTIONS

Reactions which may occur because of the solution or the technique of administration include febrile response, infection at the site of injection, venous thrombosis or phlebitis extending from the site of injection, extravasation and hypervolemia.

If an adverse reaction does occur, discontinue the infusion, evaluate the patient, institute appropriate therapeutic countermeasures and save the remainder of the fluid for examination if deemed necessary.

To report SUSPECTED ADVERSE REACTIONS, contact Fresenius Kabi USA, LLC at 1-800-551-7176 or FDA at 1-800-FDA-1088 or www.fda.gov/medwatch.

OVERDOSAGE

In the event of overhydration or solute overload, re-evaluate the patient and institute appropriate corrective measures. See WARNINGS, PRECAUTIONS, and ADVERSE REACTIONS.

DOSAGE AND ADMINISTRATION

The dose is dependent upon the age, weight and clinical condition of the patient.

As reported in the literature, the dosage and constant infusion rate of intravenous dextrose must be selected with caution in pediatric patients, particularly neonates and low birth weight infants, because of the increased risk of hyperglycemia/hypoglycemia.

Drug Interactions

Additives may be incompatible. Consult with pharmacist, if available. When introducing additives, use aseptic technique, mix thoroughly and do not store.

The presence of calcium limits their compatibility with certain drugs that form precipitates of calcium salts, and also prohibits their simultaneous infusion through the same administration set as blood because of the likelihood of coagulation.

Parenteral drug products should be inspected visually for particulate matter and discoloration prior to administration, whenever solution and container permit. See PRECAUTIONS.

HOW SUPPLIED

Lactated Ringer's and 5% Dextrose Injection, USP is supplied in single-dose freeflex® plastic containers as follows:

Product Code | Unit of Use | Unit of Sale
310241 | NDC 65219-241-00 One 1000 mL freeflex® bag | NDC 65219-241-10 Package of 10 freeflex® bags
310243 | NDC 65219-243-01 One 500 mL freeflex® bag | NDC 65219-243-50 Package of 20 freeflex® bags

Store at 20 to 25°C (68 to 77°F). [See USP Controlled Room Temperature.] Avoid excessive heat. Protect from freezing.

The container closure is not made with natural rubber latex. Non-PVC, Non-DEHP, Sterile.

INSTRUCTIONS FOR USE

Check flexible container solution composition, lot number, and expiry date.

Do not remove solution container from its overwrap until immediately before use. Use sterile equipment and aseptic technique.

Flexible Plastic Container (freeflex® bag)

To Open

1. Turn solution container over so that the text is face down. Using the pre-cut corner tabs, peel open the overwrap and remove solution container.
2. Check the solution container for leaks by squeezing firmly. If leaks are found, or if the seal is not intact, discard the solution.
3. Do not use if the solution is cloudy or a precipitate is present.

To Add Medication

1. Identify WHITE Additive Port with arrow pointing toward container.
2. Immediately before injecting additives, break off WHITE Additive Port Cap with the arrow pointing toward container.
3. Hold base of WHITE Additive Port horizontally.
4. Insert needle horizontally through the center of WHITE Additive Port's septum and inject additives.
5. Mix container contents thoroughly.

Preparation for Administration

1. Immediately before inserting the infusion set, break off BLUE Infusion Port Cap with the arrow pointing away from container.
2. Use a non-vented infusion set or close the air-inlet on a vented set.
3. Close the roller clamp of the infusion set.
4. Hold the base of BLUE Infusion Port.
5. Insert spike through BLUE Infusion Port by rotating wrist slightly until the spike is inserted.
  NOTE: See full directions accompanying administration set.

WARNING: Do not use flexible container in series connections.

Manufactured for:

Lake Zurich, Illinois 60047

Made in Norway

451770

www.fresenius-kabi.com/us

Issued: September 2022

PACKAGE LABEL

PACKAGE LABEL - PRINCIPAL DISPLAY –Lactated Ringer's and 5% Dextrose Injection, USP 1000 mL Bag Label

1000 mL NDC 65219-241-00 freeflex®

LACTATED RINGER'S and 5% DEXTROSE Injection, USP

Rx only

PACKAGE LABEL

PACKAGE LABEL - PRINCIPAL DISPLAY –Lactated Ringer's and 5% Dextrose 1000 mL Case Label

NDC 65219-241-10 310241
LACTATED RINGER'S and 5% DEXTROSE Injection, USP

1000 mL x 10

STORE AT: 20° to 25°C (68° to 77°F)
[see USP Controlled Room Temperature].

Avoid excessive heat. Protect from freezing.

PACKAGE LABEL - PRINCIPAL DISPLAY – Lactated Ringer's and 5% Dextrose Injection, USP 500 mL Bag Label

500 mL NDC 65219-243-01 freeflex®

LACTATED RINGER'S and

5% DEXTROSE

Injection, USP

Rx only

PACKAGE LABEL - PRINCIPAL DISPLAY –Lactated Ringer's and 5% Dextrose 500 mL Case Label

NDC 65219-243-50 310243

LACTATED RINGER'S and 5% DEXTROSE Injection, USP

500 mL x 20

STORE AT: 20° to 25°C (68° to 77°F)

[see USP Controlled Room Temperature].

Avoid excessive heat. Protect from freezing.